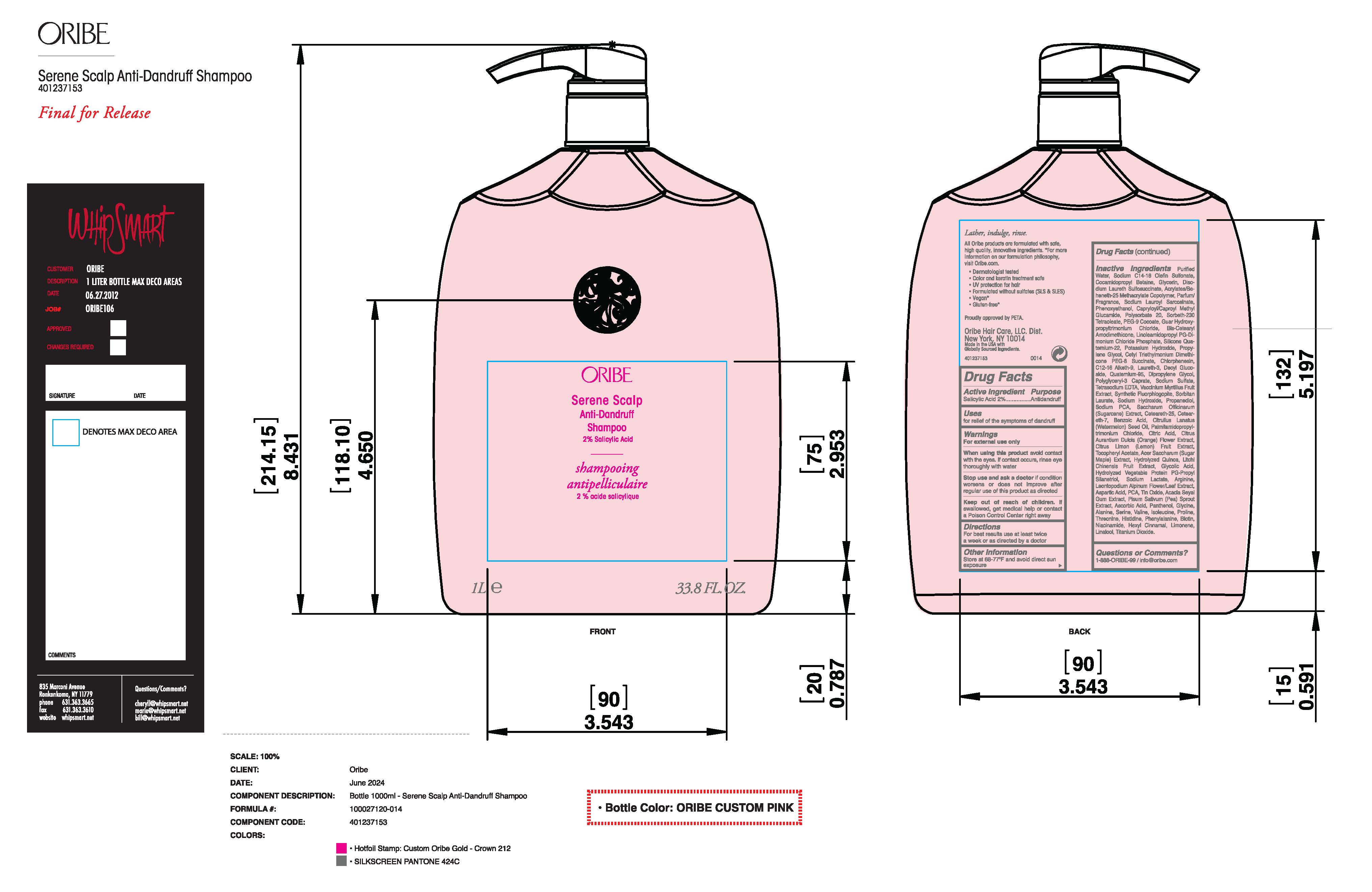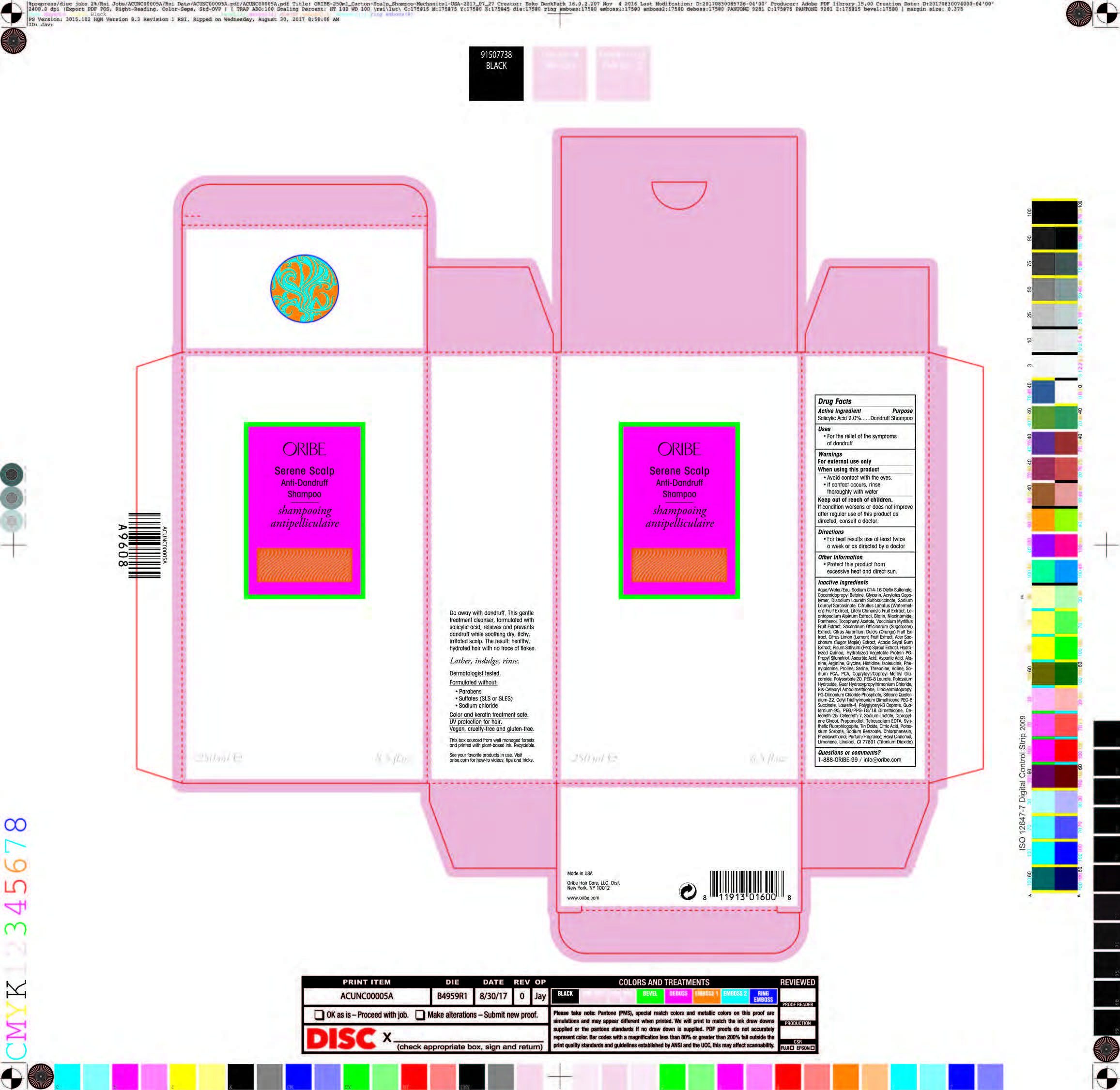 DRUG LABEL: Oribe Serene Scalp Anti Dandruff
NDC: 71438-010 | Form: LOTION
Manufacturer: Oribe Hair Care LLC
Category: otc | Type: HUMAN OTC DRUG LABEL
Date: 20260130

ACTIVE INGREDIENTS: SALICYLIC ACID 2 g/100 g
INACTIVE INGREDIENTS: WATER; SODIUM C14-16 OLEFIN SULFONATE; COCAMIDOPROPYL BETAINE; DISODIUM LAURETH SULFOSUCCINATE; SODIUM LAUROYL SARCOSINATE; CITRULLUS LANATUS VAR. LANATUS WHOLE; LITCHI CHINENSIS WHOLE; LEONTOPODIUM ALPINUM FLOWER; BIOTIN; NIACINAMIDE; PANTHENOL; TOCOPHEROL; VACCINIUM MYRTILLUS WHOLE; SACCHARUM OFFICINARUM WHOLE; ACACIA SENEGAL WHOLE; PISUM SATIVUM WHOLE; ASCORBIC ACID; ASPARTIC ACID; ALANINE; ARGININE; GLYCINE; HISTIDINE; VALINE; POLYSORBATE 20; PEG-8 LAURATE; POTASSIUM HYDROXIDE; GUAR HYDROXYPROPYLTRIMONIUM CHLORIDE (1.7 SUBSTITUENTS PER SACCHARIDE); LAURETH-4; QUATERNIUM-91; CITRIC ACID ACETATE; POTASSIUM SORBATE; SODIUM BENZOATE; PHENOXYETHANOL; TITANIUM DIOXIDE

DRUG FACTS

Active Ingredients

Salicylic Acid 2.0%

Uses

For the relief of the symptoms of dandruff

Purpose

Dandruff Shampoo

Warnings

For external use only

When using this product

• Avoid contact wilh lhe eyes.
• lf conlacl occurs, rinse thoroughly wlth water

Keep out of reach of children.

lf condition worsens or does nol improve alter regular use of this product as directed, consult a doctor.

Directions

For best resulls use ot least twice a week or as directed by a doctor

Other Information

Protect lhis product from excessive heat and direct sun.

Inactive Ingredients

Aqua/Water/Eau, Sodium C14-16 Olefin Sulfonate, Cocamidopropyl Betaine, Glycerin, Acrylates Copolymer, Disodium Laureth Sulfosuccinate, Sodium Lauroyl Sarcosinate, Citrullus Lanatus (Watermelon) Fruit Extract, Litchi Chinensis Fruit Extract, Leontopodium Alpinum Extract, Biotin, Niacinamide, Panthenol, Tocopheryl Acetate, Vaccinium Myrtillus Fruit Extract, Saccharum Officinarum (Sugarcane) Extract, Citrus Aurantium Dulcis (Orange) Fruit Extract, Citrus Limon (Lemon) Fruit Extract, Acer Saccharum (Sugar Maple) Extract, Acacia Seyal Gum Extract, Pisum Sativum (Pea) Sprout Extract, Hydrolyzed Quinoa, Hydrolyzed Vegetable Protein PG-Propyl Silanetriol, Ascorbic Acid, Aspartic Acid, Alanine, Arginine, Glycine, Histidine, Isoleucine, Phenylalanine, Proline, Serine, Threonine, Valine, Sodium PCA, PCA, Capryloyl/Caproyl Methyl Glucamide, Polysorbate 20, PEG-8 Laurate, Potassium Hydroxide, Guar Hydroxypropyltrimonium Chloride, Bis-Cetearyl Amodimethicone, Linoleamidopropyl PG-Dimonium Chloride Phosphate, Silicone Quaternium-22, Cetyl Triethylmonium Dimethicone PEG-8 Succinate, Laureth-4, Polyglyceryl-3 Caprate, Quaternium-95, PEG/PPG-18/18 Dimethicone, Ceteareth-25, Ceteareth-7, Sodium Lactate, Dipropylene Glycol, Propanediol, Tetrasodium EDTA, Synthetic Fluorphlogopite, Tin Oxide, Citric Acid, Potassium Sorbate, Sodium Benzoate, Chlorphenesin, Phenoxyethanol, Parfum/Fragrance, Hexyl Cinnamal, Limonene, Linalool, CI 77891 (Titanium Dioxide)

Questions or Comments?

1-888-0RIBE-99 / info@oribe.com